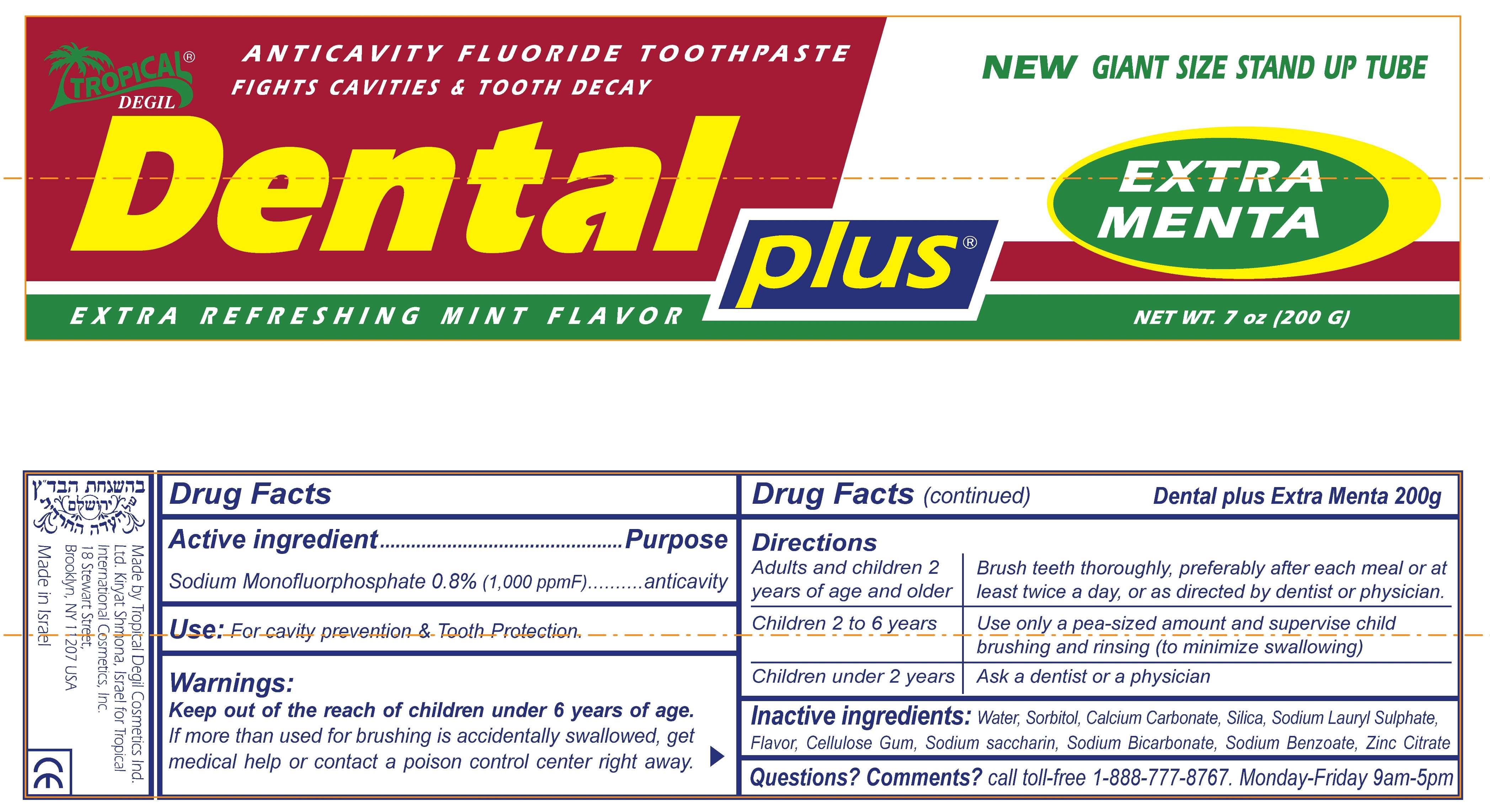 DRUG LABEL: Dental plus Extra Menta
NDC: 62678-206 | Form: PASTE, DENTIFRICE
Manufacturer: Tropical International Manufacturing Inc
Category: otc | Type: HUMAN OTC DRUG LABEL
Date: 20100519

ACTIVE INGREDIENTS: SODIUM MONOFLUOROPHOSPHATE 8 mg/1 g

Drug facts

Active Ingredient

Sodium Monofluorophosphate 0.8% (1,000 ppmF)

Purpose

anticavity

Use

For cavity prevention and tooth protection.

Warnings

Keep out of the reach of children under 6 years of age.

If more than used for brushing is accidentally swallowed, get medical help or contact a poison control center right away.

Drug Facts (continued)

Dental plus Extra Menta 200 g

Directions

Adults and children 2 years of age and older
Children 2 to 6 years
Children under 2 years

Brush teeth thoroughly, preferably after each meal or at least twice a day, or as directed by dentist or physician.
Use only a pea-sized amount and supervise child brushing and rinsing (to minimize swallowing)
Ask a dentist or a physician

Inactive ingredients

Water, Sorbitol, Calcium Carbonate, Silica, Sodium Lauryl Sulphate, Flavor, Cellulose Gum, Sodium saccharin, Sodium Bicarbonate, Sodium Benzoate, Zinc Citrate

Questions? Comments?

call toll-free 1-888-777-8767. Monday-Friday 9am-5pm

Made by Tropical Degil Cosmetics

Ind. Ltd. Kiryat Shmona, Israel for

Tropical International Cosmetics, Inc.

18 Stewart Street,

Brooklyn, NY 11207 USA

Made in Israel

PRINCIPAL DISPLAY PANEL - 7 oz Tube

ANTICAVITY FLUORIDE TOOTHPASTE

FIGHTS CAVITIES and TOOTH DECAY

Tropical DEGIL Dental plus EXTRA MENTA

NEW GIANT SIZE STAND UP TUBE

EXTRA REFRESHING MINT FLAVOR

NET WT. 7 OZ (200 G)